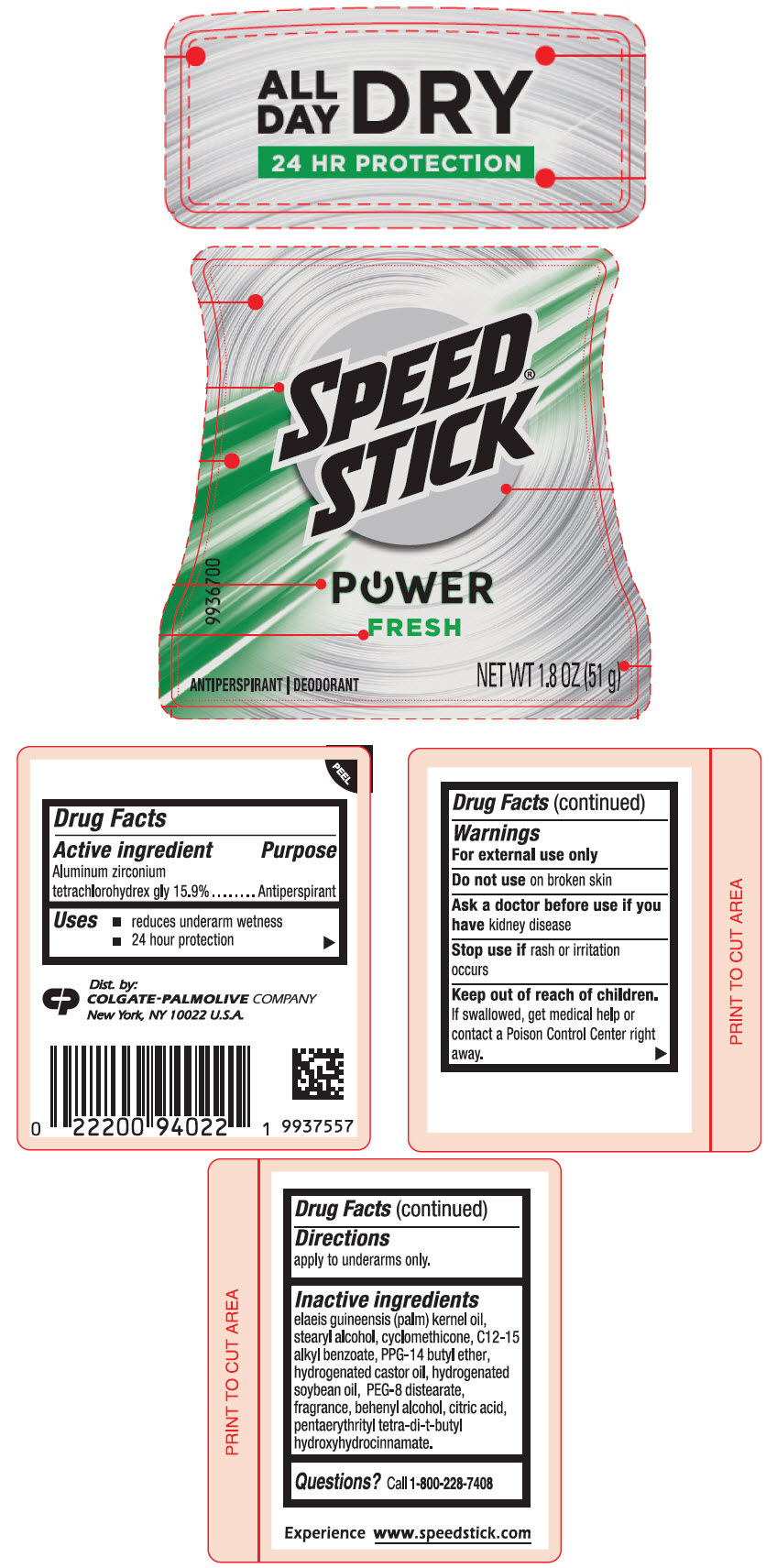 DRUG LABEL: Speed Stick  Power Fresh
NDC: 35000-864 | Form: STICK
Manufacturer: Colgate-Palmolive Company
Category: otc | Type: HUMAN OTC DRUG LABEL
Date: 20250402

ACTIVE INGREDIENTS: ALUMINUM ZIRCONIUM TETRACHLOROHYDREX GLY 159 mg/1 g
INACTIVE INGREDIENTS: PALM KERNEL OIL; STEARYL ALCOHOL; CYCLOMETHICONE 5; ALKYL (C12-15) BENZOATE; PPG-14 BUTYL ETHER; HYDROGENATED CASTOR OIL; HYDROGENATED SOYBEAN OIL; PEG-8 DISTEARATE; DOCOSANOL; CITRIC ACID MONOHYDRATE; PENTAERYTHRITOL TETRAKIS(3-(3,5-DI-TERT-BUTYL-4-HYDROXYPHENYL)PROPIONATE)

Speed® Stick Power Fresh
Power Fresh

Drug Facts

Active ingredient

Aluminum zirconium tetrachlorohydrex gly 15.9%

Purpose

Antiperspirant

Uses

- reduces underarm wetness
- 24 hour protection

Warnings

For external use only

Do not use on broken skin

Ask a doctor before use if you have kidney disease

Stop use if rash or irritation occurs

Keep out of reach of children. If swallowed, get medical help or contact a Poison Control Center right away.

Directions

apply to underarms only.

Inactive ingredients

elaeis guineensis (palm) kernel oil, stearyl alcohol, cyclomethicone, C12-15 alkyl benzoate, PPG-14 butyl ether, hydrogenated castor oil, hydrogenated soybean oil, PEG-8 distearate, fragrance, behenyl alcohol, citric acid, pentaerythrityl tetra-di-t-butyl hydroxyhydrocinnamate.

Questions?

Call 1-800-228-7408

Dist. by:
COLGATE-PALMOLIVE COMPANY
New York, NY 10022 U.S.A.

PRINCIPAL DISPLAY PANEL - 51 g Container Label

ALL
DAY
DRY
24 HR PROTECTION

SPEED®
STICK

POWER
FRESH

ANTIPERSPIRANT | DEODORANT

NET WT 1.8 OZ (51 g)

9936700